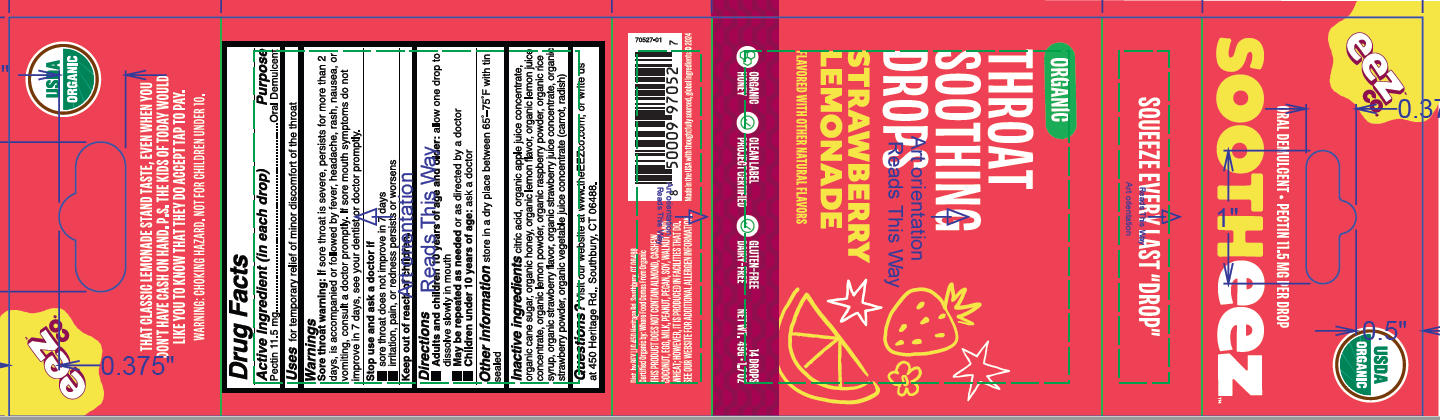 DRUG LABEL: Sootheez Strawberry Lemonade
NDC: 61584-018 | Form: LOZENGE
Manufacturer: Primrose Candy Co.
Category: otc | Type: HUMAN OTC DRUG LABEL
Date: 20260202

ACTIVE INGREDIENTS: PECTIN 11.5 mg/3.5 g
INACTIVE INGREDIENTS: APPLE JUICE; FRAGARIA ANANASSA (STRAWBERRY) FRUIT POWDER; SUCROSE; HONEY; LEMON; STRAWBERRY JUICE; WHITE RICE; CITRIC ACID; RASPBERRY; RADISH; CARROT JUICE; LEMON JUICE

Sootheez Strawberry Lemonade

Active ingredient

Pectin 11.5mg

Purpose

Oral Demulcent

Uses

Uses for temporary relief of minor discomfort of the throat.

Warnings

Sore throat warning: If sore throat is severe, persists for more than 2 days, is accompanied or followed by fever, headache, rash, nuasea, or vomiting, consult a doctor promptly. If sore mouth symptoms, do not improve in 7 days, see your denist or doctor promptly.

Stop use and ask a doctor if

- sore throat does not improve in 7 days
- irritation, pain, or redness persists or worsens.

Keep out of reach of children

Directions

- Adukts and children 10 years of age and older: allow one drop to dissolve slowly in mouth
- May be repeated as needed or as directed by a doctor
- Children under 10 years of age: ask a doctor

Other information

store in a dry place between 65-75F with in sealed.

Inactive ingredients

citric acid

organic apple juice concentrate

organic cane sugar

organic honey

organic lemon flavor

organic lemon juice concentrate

organic lemon powder

organic raspberry powder

organic rice syrup

organic strawberry juice concentrate

organic strawberry powder

organic vegetable juice concentrate (carrot, radish)